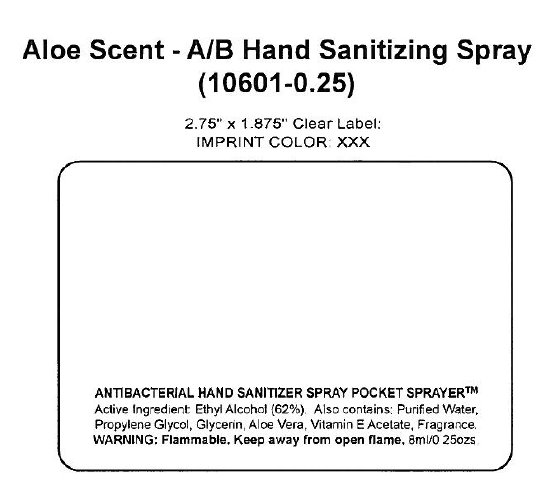 DRUG LABEL: Aloe Scent A B Hand Sanitizing
NDC: 42825-100 | Form: SPRAY
Manufacturer: Custom HBC Corporation
Category: otc | Type: HUMAN OTC DRUG LABEL
Date: 20100625

ACTIVE INGREDIENTS: ALCOHOL 62 mL/100 mL

Aloe Scent - A/B Hand Sanitizing Spray

Active Ingredient:

Ethyl Alcohol (62 percent)

INACTIVE INGREDIENT

Also contains: Purified Water, Propylene Glycol, Glycerin, Aloe Vera, Vitamin E Acetate, Fragrance.

Warning:

Flammable. Keep away from open flame

DESCRIPTION

8ml / 0.25 ozs

PACKAGE LABEL

Aloe Scent - A/B Hand Sanitizing Spray

(10601-0.25)